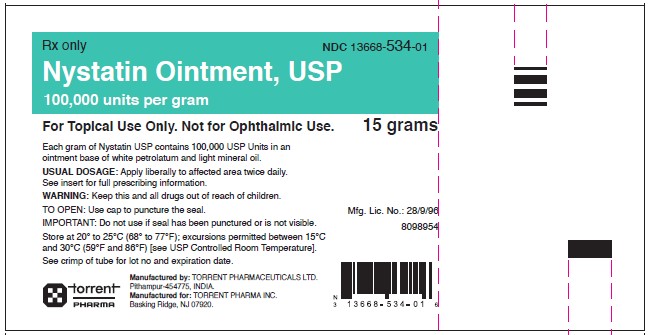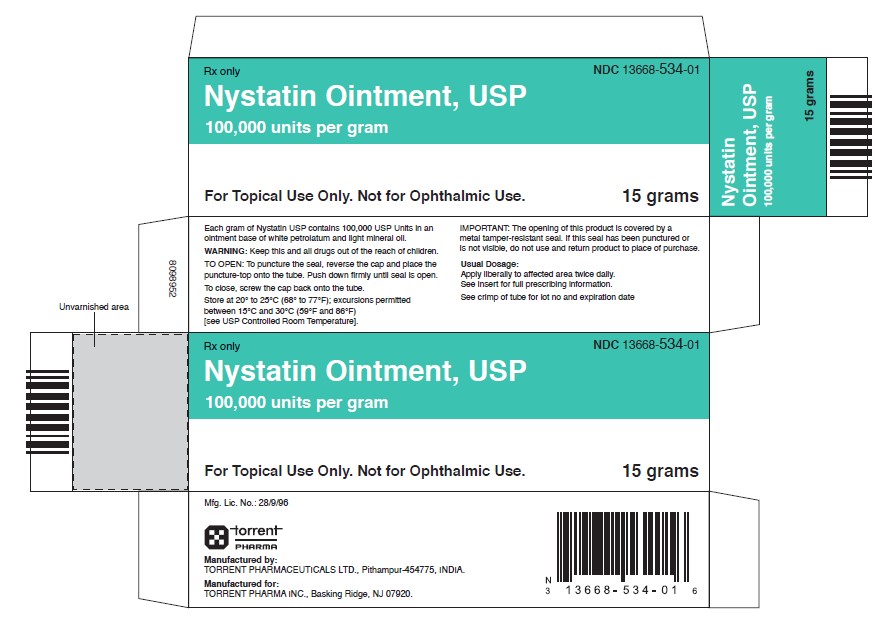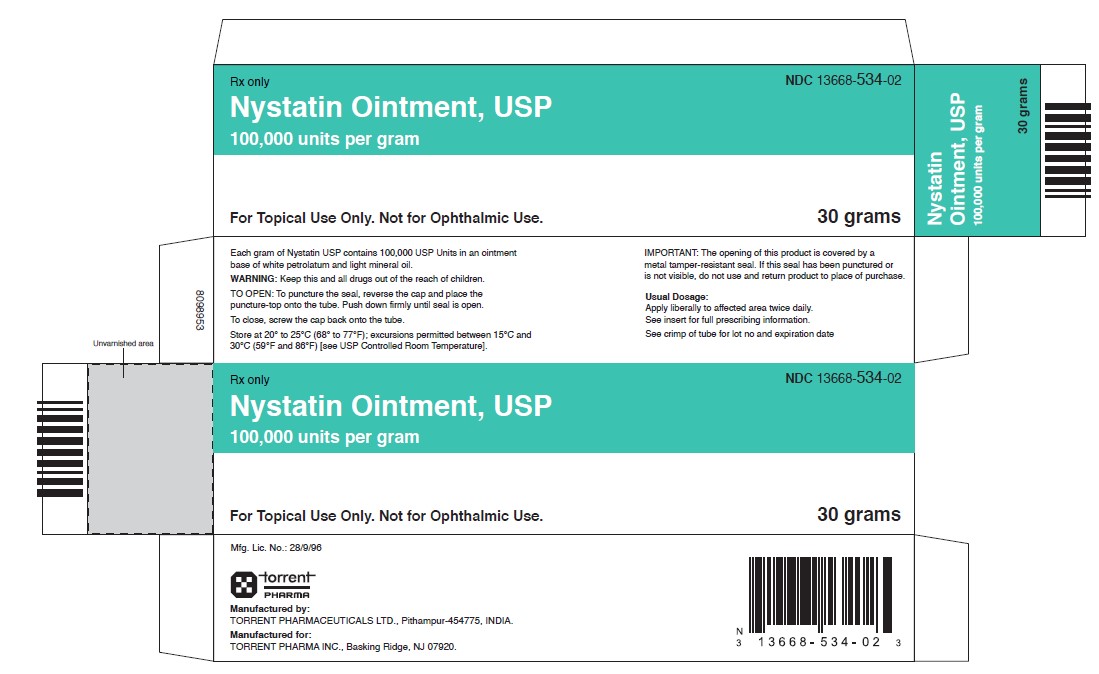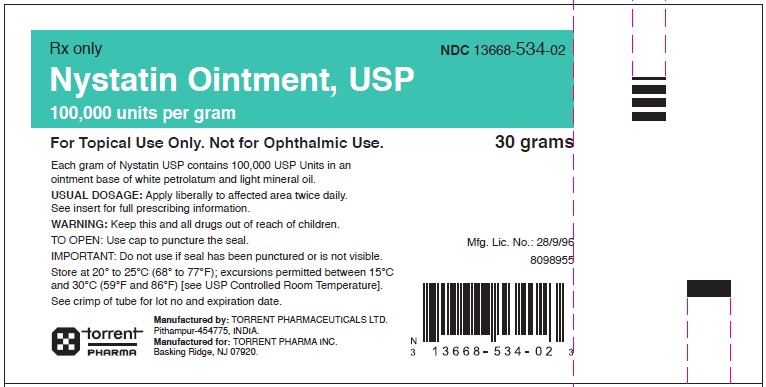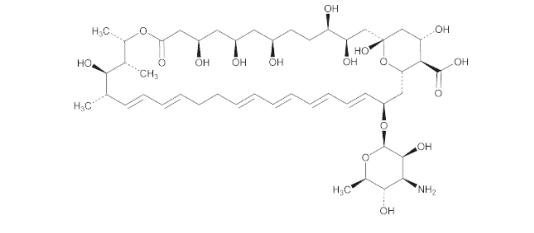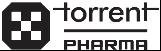 DRUG LABEL: Nystatin
NDC: 13668-534 | Form: OINTMENT
Manufacturer: Torrent Pharmaceuticals Limited
Category: prescription | Type: HUMAN PRESCRIPTION DRUG LABEL
Date: 20241206

ACTIVE INGREDIENTS: NYSTATIN 100000 U/1 g
INACTIVE INGREDIENTS: LIGHT MINERAL OIL; PETROLATUM

NYSTATIN OINTMENT, USP
For Topical Use Only. Not for Ophthalmic Use.

DESCRIPTION

Nystatin is a polyene antifungal antibiotic drug obtained from Streptomyces nursei.

Structural formula:

Molecular formula | : | C47H75NO17
Molecular weight | : | 926.09 g/mol

Nystatin ointment is for dermatologic use. Nystatin ointment for topical use contains 100,000 USP nystatin units per gram in an ointment base of light mineral oil and white petrolatum.

CLINICAL PHARMACOLOGY

Pharmacokinetics

Nystatin is not absorbed from intact skin or mucous membrane.

Microbiology

Nystatin is an antibiotic which is both fungistatic and fungicidal in vitro against a wide variety of yeasts and yeast-like fungi, including Candida albicans, C. parapsilosis, C. tropicalis, C. guilliermondi, C. pseudotropicalis, C. krusei, Torulopsis glabrata, Tricophyton rubrum, T. mentagrophytes.

Nystatin acts by binding to sterols in the cell membrane of susceptible species resulting in a change in membrane permeability and the subsequent leakage of intracellular components. On repeated subculturing with increasing concentrations of nystatin, Candida albicans does not develop resistance to nystatin. Generally, resistance to nystatin does not develop during therapy. However, other species of Candida (C. tropicalis, C. guilliermondi, C. krusei, and C. stellatoides) become quite resistant on treatment with nystatin and simultaneously become cross resistant to amphotericin as well. This resistance is lost when the antibiotic is removed.

Nystatin exhibits no appreciable activity against bacteria, protozoa, or viruses.

INDICATIONS AND USAGE

Nystatin ointment is indicated in the treatment of cutaneous or mucocutaneous mycotic infections caused by Candida albicans and other susceptible Candida species.

Nystatin ointment is not indicated for systemic, oral, intravaginal or ophthalmic use.

CONTRAINDICATIONS

Nystatin ointment is contraindicated in patients with a history of hypersensitivity to any of their components.

PRECAUTIONS

General

Nystatin ointment should not be used for the treatment of systemic, oral, intravaginal or ophthalmic infections.

If irritation or sensitization develops, treatment should be discontinued and appropriate measures taken as indicated. It is recommended that KOH smears, cultures, or other diagnostic methods be used to confirm the diagnosis of cutaneous or mucocutaneous candidiasis and to rule out infection caused by other pathogens.

INFORMATION FOR PATIENTS

Patients using these medications should receive the following information and instructions:

1. The patient should be instructed to use these medications as directed (including the replacement of missed doses). These medications are not for any disorder other than that for which they are prescribed.

2. Even if symptomatic relief occurs within the first few days of treatment, the patient should be advised not to interrupt or discontinue therapy until the prescribed course of treatment is completed.

3. If symptoms of irritation develop, the patient should be advised to notify the physician promptly.

Laboratory Tests

If there is a lack of therapeutic response, KOH smears, cultures, or other diagnostic methods should be repeated.

Carcinogenesis, Mutagenesis, Impairment of Fertility

No long-term animal studies have been performed to evaluate the carcinogenic potential of nystatin. No studies have been performed to determine the mutagenicity of nystatin or its effects on male or female fertility.

Pregnancy: Teratogenic Effects

Category C. Animal reproduction studies have not been conducted with any nystatin topical preparation. It also is not known whether these preparations can cause fetal harm when used by a pregnant woman or can affect reproductive capacity. Nystatin topical preparations should be prescribed for a pregnant woman only if the potential benefit to the mother outweighs the potential risk to the fetus.

Nursing Mothers

It is not known whether nystatin is excreted in human milk. Caution should be exercised when nystatin is prescribed for a nursing woman.

Pediatric Use

Safety and effectiveness have been established in the pediatric population from birth to 16 years.

See DOSAGE AND ADMINISTRATION

ADVERSE REACTIONS

The frequency of adverse events reported in patients using nystatin ointment preparations is less than 0.1%. The more common events that were reported include allergic reactions, burning, itching, rash, eczema, and pain on application.

(See PRECAUTIONS: General.)

DOSAGE AND ADMINISTRATION

Nystatin Ointment

Adults and Pediatric Patients (Neonates and Older):

Apply liberally to affected areas twice daily or as indicated until healing is complete.

HOW SUPPLIED

Nystatin ointment USP, 100,000 units per gram is a pale yellow to yellow color ointment available as follows:

NDC 13668-534-01 15 gram tube

NDC 13668-534-02 30 gram tube

STORAGE

Store at 20° to 25°C (68° to 77°F); excursions permitted between 15°C and 30°C (59°F and 86°F) [see USP Controlled Room Temperature].

Manufactured by:

TORRENT PHARMACEUTICALS LTD., Pithampur-454775, INDIA .

Manufactured for:

TORRENT PHARMA INC., Basking Ridge, NJ 07920

8063926 Revised June 2018

PACKAGE LABEL.PRINCIPAL DISPLAY PANEL

Nystatin Ointment, USP 15 grams (Tube label)

Nystatin Ointment, USP 15 grams (Carton label)

Nystatin Ointment, USP 30 grams (Tube label)

Nystatin Ointment, USP 30 grams (carton label)